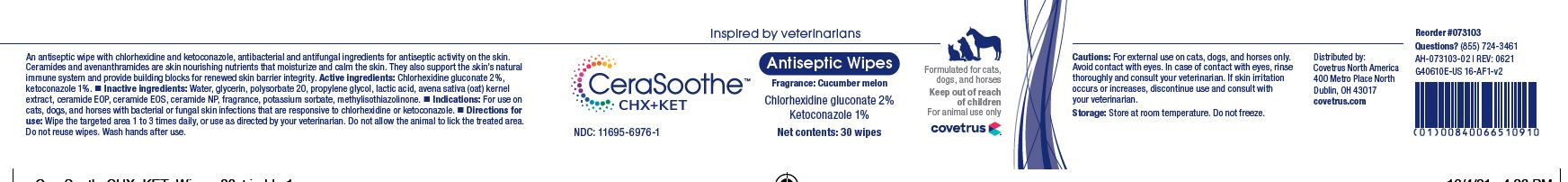 DRUG LABEL: CeraSoothe
NDC: 11695-6976 | Form: SWAB
Manufacturer: Butler Animal Health Supply, LLC dba Covetrus North America
Category: animal | Type: OTC ANIMAL DRUG LABEL
Date: 20220518

ACTIVE INGREDIENTS: CHLORHEXIDINE GLUCONATE 20 mg/1 1; KETOCONAZOLE 10 mg/1 1
INACTIVE INGREDIENTS: WATER; GLYCERIN; POLYSORBATE 20; PROPYLENE GLYCOL; LACTIC ACID; AVENANTHRAMIDES; CERAMIDE NP; POTASSIUM SORBATE; METHYLISOTHIAZOLINONE

DESCRIPTION

CeraSoothe CHX+KET

ANTISEPTIC WIPES

ACTIVE INGREDIENTS: Chlorhexidine gluconate 2%, Ketoconazole 1%.

INACTIVE INGREDIENTS: Water, glycerin, polysorbate 20, propylene glycol, lactic acid, avena sativa (oat) kernal extract, ceramide EOP, ceramide EOS, ceramide NP, fragrance, potassium sorbate, methylisothiazolinone.

INDICATIONS AND USAGE

INDICATIONS: For use on cats, dogs, and horses with bacterial or fungal skins infections that are responsive to chlorhexidine or ketoconazole.

DIRECTIONS FOR USE: Wipe the targeted area 1 to 3 times daily, or use as directed by your veterinarian. Do not allow the animal to lick the treated area. Do not reuse wipes. Wash hands after use.

WARNINGS AND PRECAUTIONS

CAUTIONS: For external use on cats, dogs, and horses only. Avoid contact with eyes. In case of contact with eyes, rinse thoroughly and consult your veterinarian. If skin irritation occurs or increases, discontinue use and consult with your veterinarian.

WARNING: Keep out of reach of children.

STORAGE: Store at room temperature. Do not freeze.

Distributed by:

Covetrus North America

400 Metro Place North

Dublin, OH 43017

covetrus.com

QUESTIONS? 1-800-999-029

PRINCIPAL DISPLAY PANEL - 30 Count Canister

Inspired by veterinarians

CeraSoothe CHX+KET

Antiseptic Wipes

Fragrance: Cucumber melon

Chlorhexidine gluconate 2%

Ketoconazole 1%

Formulated cats, dogs, and horses

Keep out of reach of children

For animal use only

NDC 11695-6976-1

Net Contents: 30 Wipes